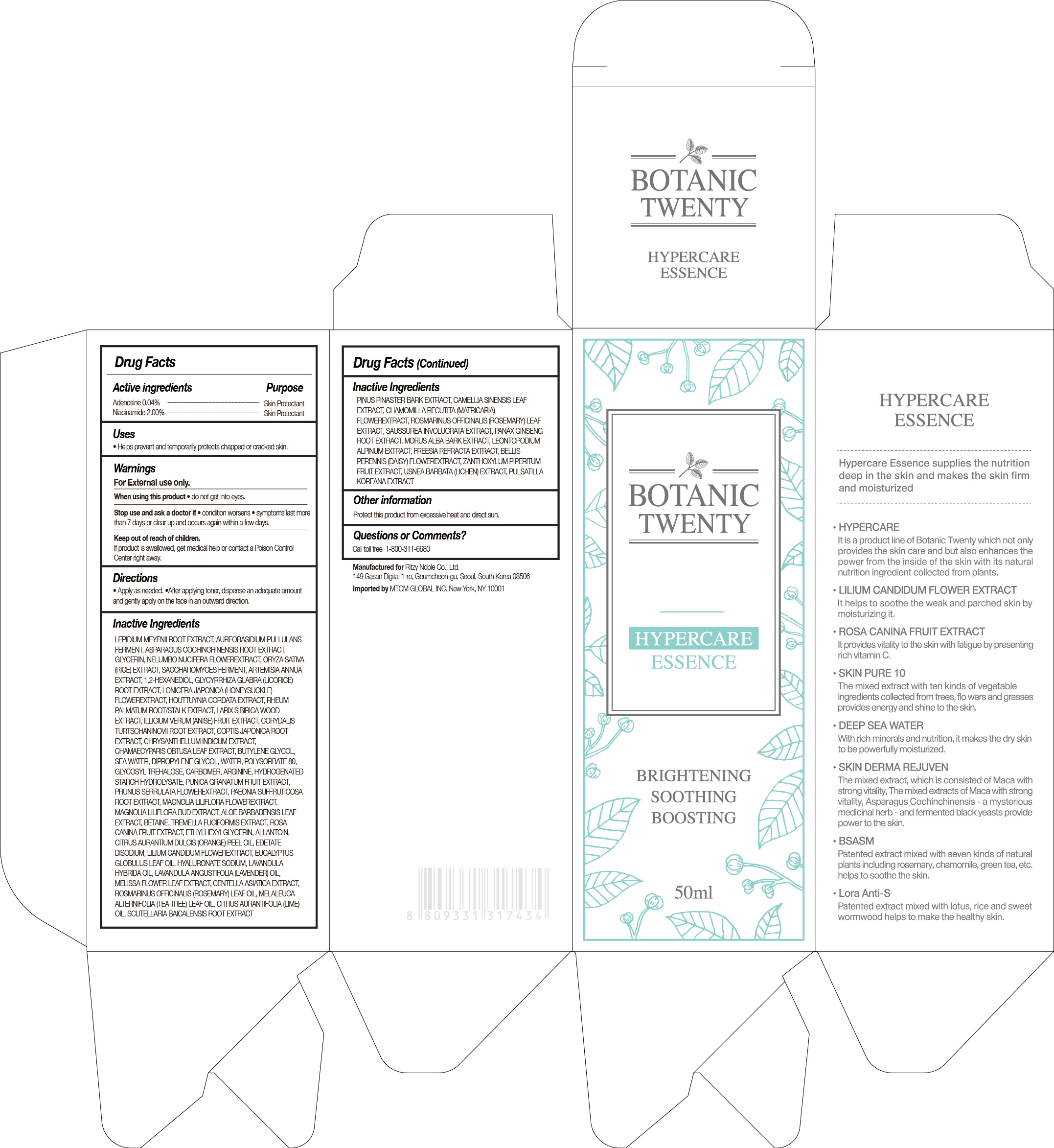 DRUG LABEL: BOTANIC TWENTY HYPERCARE ESSENCE
NDC: 71364-101 | Form: GEL
Manufacturer: RITZY NOBLE CO., LTD.
Category: otc | Type: HUMAN OTC DRUG LABEL
Date: 20180101

ACTIVE INGREDIENTS: ADENOSINE 0.04 g/150 mL; NIACINAMIDE 2 g/150 mL
INACTIVE INGREDIENTS: BETAINE; 1,2-HEXANEDIOL; DIPROPYLENE GLYCOL; NELUMBO NUCIFERA FLOWER; ARTEMISIA ANNUA WHOLE; SACCHAROMYCES LYSATE; ARGININE; COPTIS JAPONICA ROOT; CHAMAECYPARIS OBTUSA LEAF; RHEUM PALMATUM ROOT; BUTYLENE GLYCOL; LEPIDIUM MEYENII ROOT; AUREOBASIDIUM PULLULANS VAR. PULLUTANS; WATER; GLYCERIN; LONICERA JAPONICA FLOWER; CHRYSANTHEMUM INDICUM FLOWER; CORYDALIS TURTSCHANINOVII WHOLE; ILLICIUM VERUM WHOLE; LARIX SIBIRICA WOOD; ETHYLHEXYLGLYCERIN; CITRUS AURANTIUM FRUIT OIL; CENTELLA ASIATICA; EUCALYPTUS GLOBULUS LEAF; LAVANDULA ANGUSTIFOLIA FLOWER; PINUS PINASTER WOOD; SCUTELLARIA BAICALENSIS ROOT; ROSMARINUS OFFICINALIS FLOWERING TOP OIL; MELALEUCA ALTERNIFOLIA LEAF; ROSMARINUS OFFICINALIS WHOLE; BELLIS PERENNIS FLOWER; FREESIA ALBA FLOWER; LEONTOPODIUM ALPINUM; LILIUM CANDIDUM FLOWER; MORUS ALBA BARK; PANAX GINSENG ROOT WATER; MAGNOLIA LILIIFLORA FLOWER; PUNICA GRANATUM SEED; EDETATE DISODIUM; SAUSSUREA INVOLUCRATA FLOWERING TOP; ASPARAGUS COCHINCHINENSIS WHOLE; HOUTTUYNIA CORDATA TOP; ORYZA SATIVA WHOLE; ALOE VERA LEAF; GLYCYRRHIZA GLABRA; POLYSORBATE 80; ALLANTOIN

Botanic Twenty Hypercare Essence

ACTIVE INGREDIENTS

ADENOSINE 0.04%

NIACINAMIDE 2.00%

PURPOSE

SKIN PROTECTANT

USES

Helps prevent and temporarily protects chapped or cracked skin.

WARNINGS

FOR EXTERNAL USE ONLY

WHEN USING THIS PRODUCT

• do not get into eyes.

STOP USE AND ASK A DOCTOR IF

• condition worsens

• symptoms last more than 7 days or clear up and occurs again within a few days.

KEEP OUT OF REACH OF CHILDREN

If product is swallowed, get medical help or contact a Poison Control Center right away.

DIRECTIONS

• Apply as needed.

• After applying toner, dispense an adequate amount and gently apply on the face in an outward direction.

INACTIVE INGREDIENTS

LEPIDIUM MEYENII ROOT EXTRACT, AUREOBASIDIUM PULLULANS FERMENT, ASPARAGUS COCHINCHINENSIS ROOT EXTRACT, GLYCERIN, NELUMBO NUCIFERA FLOWEREXTRACT, ORYZA SATIVA (RICE) EXTRACT, SACCHAROMYCES FERMENT, ARTEMISIA ANNUA EXTRACT, 1,2-HEXANEDIOL, GLYCYRRHIZA GLABRA (LICORICE) ROOT EXTRACT, LONICERA JAPONICA (HONEYSUCKLE) FLOWEREXTRACT, HOUTTUYNIA CORDATA EXTRACT, RHEUM PALMATUM ROOT/STALK EXTRACT, LARIX SIBIRICA WOOD EXTRACT, ILLICIUM VERUM (ANISE) FRUIT EXTRACT, CORYDALIS TURTSCHANINOVII ROOT EXTRACT, COPTIS JAPONICA ROOT EXTRACT, CHRYSANTHELLUM INDICUM EXTRACT, CHAMAECYPARIS OBTUSA LEAF EXTRACT, BUTYLENE GLYCOL, SEA WATER, DIPROPYLENE GLYCOL, WATER, POLYSORBATE 80, GLYCOSYL TREHALOSE, CARBOMER, ARGININE, HYDROGENATED STARCH HYDROLYSATE, PUNICA GRANATUM FRUIT EXTRACT, PRUNUS SERRULATA FLOWEREXTRACT, PAEONIA SUFFRUTICOSA ROOT EXTRACT, MAGNOLIA LILIFLORA FLOWEREXTRACT, MAGNOLIA LILIFLORA BUD EXTRACT, ALOE BARBADENSIS LEAF EXTRACT, BETAINE, TREMELLA FUCIFORMIS EXTRACT, ROSA CANINA FRUIT EXTRACT, ETHYLHEXYLGLYCERIN, ALLANTOIN, CITRUS AURANTIUM DULCIS (ORANGE) PEEL OIL, EDETATE DISODIUM, LILIUM CANDIDUM FLOWEREXTRACT, EUCALYPTUS GLOBULUS LEAF OIL, HYALURONATE SODIUM, LAVANDULA HYBRIDA OIL, LAVANDULA ANGUSTIFOLIA (LAVENDER) OIL, MELISSA FLOWER LEAF EXTRACT, CENTELLA ASIATICA EXTRACT, ROSMARINUS OFFICINALIS (ROSEMARY) LEAF OIL, MELALEUCA ALTERNIFOLIA (TEA TREE) LEAF OIL, CITRUS AURANTIFOLIA (LIME) OIL, SCUTELLARIA BAICALENSIS ROOT EXTRACT, PINUS PINASTER BARK EXTRACT, CAMELLIA SINENSIS LEAF EXTRACT, CHAMOMILLA RECUTITA (MATRICARIA) FLOWEREXTRACT, ROSMARINUS OFFICINALIS (ROSEMARY) LEAF EXTRACT, SAUSSUREA INVOLUCRATA EXTRACT, PANAX GINSENG ROOT EXTRACT, MORUS ALBA BARK EXTRACT, LEONTOPODIUM ALPINUM EXTRACT, FREESIA REFRACTA EXTRACT, BELLIS PERENNIS (DAISY) FLOWEREXTRACT, ZANTHOXYLUM PIPERITUM FRUIT EXTRACT, USNEA BARBATA (LICHEN) EXTRACT, PULSATILLA KOREANA EXTRACT

OTHER INFORMATION

Protect this product from excessive heat and direct sun.

QUESTIONS OR COMMENTS?

Call toll free 1-800-311-6680